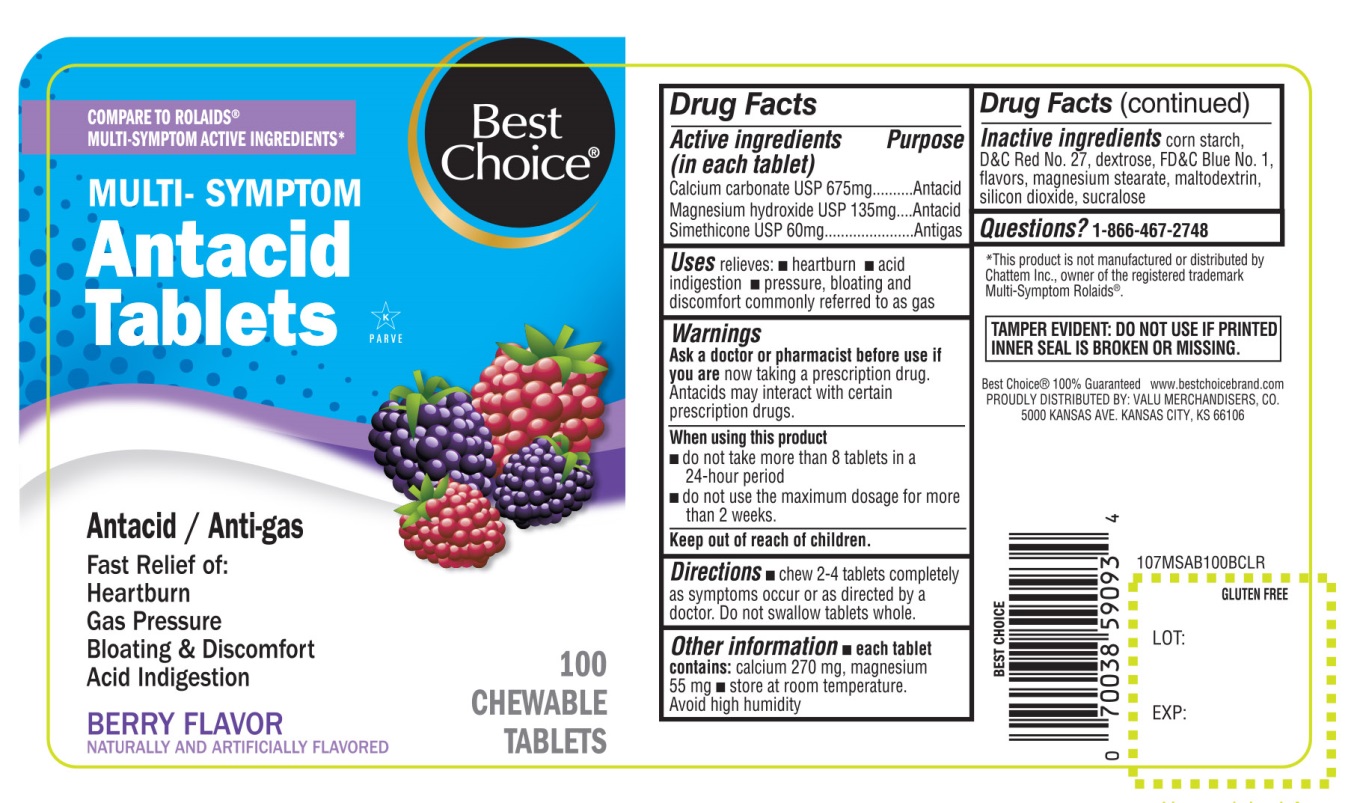 DRUG LABEL: Best Choice Extra Strength

NDC: 63941-107 | Form: TABLET, CHEWABLE
Manufacturer: BEST CHOICE (VALU MERCHANDISERS COMPANY)
Category: otc | Type: HUMAN OTC DRUG LABEL
Date: 20250716

ACTIVE INGREDIENTS: CALCIUM CARBONATE 675 mg/1 1; MAGNESIUM HYDROXIDE 135 mg/1 1; DIMETHICONE, UNSPECIFIED 60 mg/1 1
INACTIVE INGREDIENTS: STARCH, CORN; D&C RED NO. 27; DEXTROSE, UNSPECIFIED FORM; FD&C BLUE NO. 1; MAGNESIUM STEARATE; MALTODEXTRIN; SILICON DIOXIDE; SUCRALOSE

Best Choice® Multi Symptom 100 Chewable Tablets Berry Flavor

Drug Facts

Active ingredients(in each tablet)

Calcium Carbonate USP 675 mg
Magnesium hydroxide USP 135 mg

Simethicone USP 60mg

Purpose

Antacid

Antacid

Antigas

Uses

relieves:

- heartburn
- acid indigestion
- pressure, bloating and discomfort commonly referred to as gas

Warnings

Ask a doctor or pharmacist before use if you are

now taking a prescription drug. Antacids may interact with certain prescription drugs.

When using this product

- do not take more than 8 tablets in a 24-hour period
- do not use the maximum dosage for more than 2 weeks

Directions

- chew 2-4 tablets completely as symptoms occur or as directed by a doctor. Do not swallow tablets whole.

Other information

- each tablet contains:calcium 270 mg, magnesium 55 mg
- store at room temperature

Avoid high humidity

Inactive ingredients

corn starch, D&C Red 27 lake, dextrose, FD&C Blue 1 lake, flavor, magnesium stearate, maltodextrin, silicon dioxide, sucralose.

Questions or comments?

1-866-467-2748

PRINCIPAL DISPLAY PANEL

NDC# 63941-107-10

COMPARE TO ROLAIDS®MULTI-SYMPTOMS ACTIVE INGREDIENTS*

Best Choice®

MULTI-SYMPTOM

Antacid & Anti-gas Tablets

Calcium & Magnesium Rich

Antacid/Anti-gas

Fast Relief of:

- Heartburn
- Gas Pressure
- Bloating & Discomfort
- Acid Indigestion

BERRY FLAVOR

NATURALLY AND ARTFICIALLY FLAVORED

100 CHEWABLE TABLETS

GLUTEN-FREE

K PAREVE

Best Choice®100% Guaranteed www.bestchoicebrand.com

PROUDLY DISTRIBUTED BY: VALU MERCHANDISERS, CO.

500 KANSAN AVE. KANSAS CITY, KS 66106

*This product is not manufactured or distributed by Chattem Inc., owner of the registered trademark ROLAIDS®

TAMPER EVIDENT: DO NOT USE IF PRINTED INNER SEAL IS BROKEN OR MISSING.